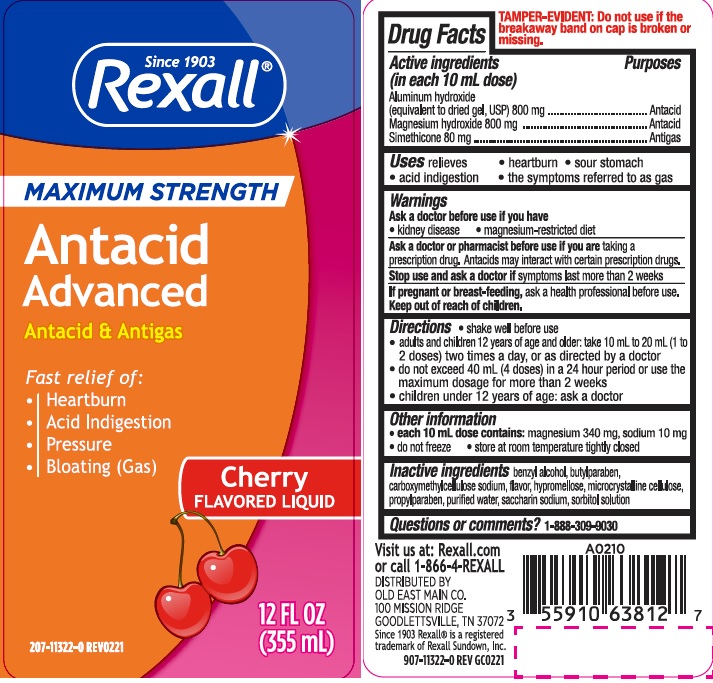 DRUG LABEL: MAXIMUM STRENGTH ADVANCED ANTACID
NDC: 55910-638 | Form: LIQUID
Manufacturer: DOLGENCORP, LLC
Category: otc | Type: HUMAN OTC DRUG LABEL
Date: 20231107

ACTIVE INGREDIENTS: ALUMINUM HYDROXIDE 800 mg/10 mL; MAGNESIUM HYDROXIDE 800 mg/10 mL; DIMETHICONE 80 mg/10 mL
INACTIVE INGREDIENTS: BENZYL ALCOHOL; BUTYLPARABEN; CARBOXYMETHYLCELLULOSE SODIUM; HYPROMELLOSES; CELLULOSE, MICROCRYSTALLINE; PROPYLPARABEN; WATER; SACCHARIN SODIUM; SORBITOL SOLUTION

dg ant max cherry

Active ingredients (in each 10 mL dose)

Aluminum hydroxide (equivalent to dried gel, USP) 800 mg

Magnesium hydroxide 800 mg

Simethicone 80 mg

Purposes

Antacid

Antigas

Uses

relieves

- heartburn
- sour stomach
- acid indigestion
- symptoms referred to as gas

Warnings

Ask a doctor before use if you have

• kidney disease

• a magnesium-restricted diet

Ask a doctor or pharmacist before use if you are presently taking a prescription drug.

Antacids may interact with certain prescription drugs.

Stop use and ask a doctor if symptoms last more than 2 weeks

If pregnant or breast-feeding, ask a health professional before use.

Keep out of reach of children.

Directions

- shake well before use
- adults and children 12 years of age and older: take 10ml to 20ml (1 to 2 doses) two times a day or as directed by a doctor
- do not exceed 40ml (4 doses) in a 24 hour period or use the maximum dosage for more than 2 weeks
- children under 12 years of age: ask a doctor

Other information

- each 10 mL dose contains: magnesium 340 mg, sodium 10 mg
- do not freeze
- store at room temperature tightly closed

Inactive ingredients

benzyl alcohol, butylparaben, carboxymethylcellulose sodium, flavor, hypromellose, microcrystalline cellulose, propylparaben, purified water, saccharin sodium, sorbitol solution

Questions or Comments?

1-888-309-9030